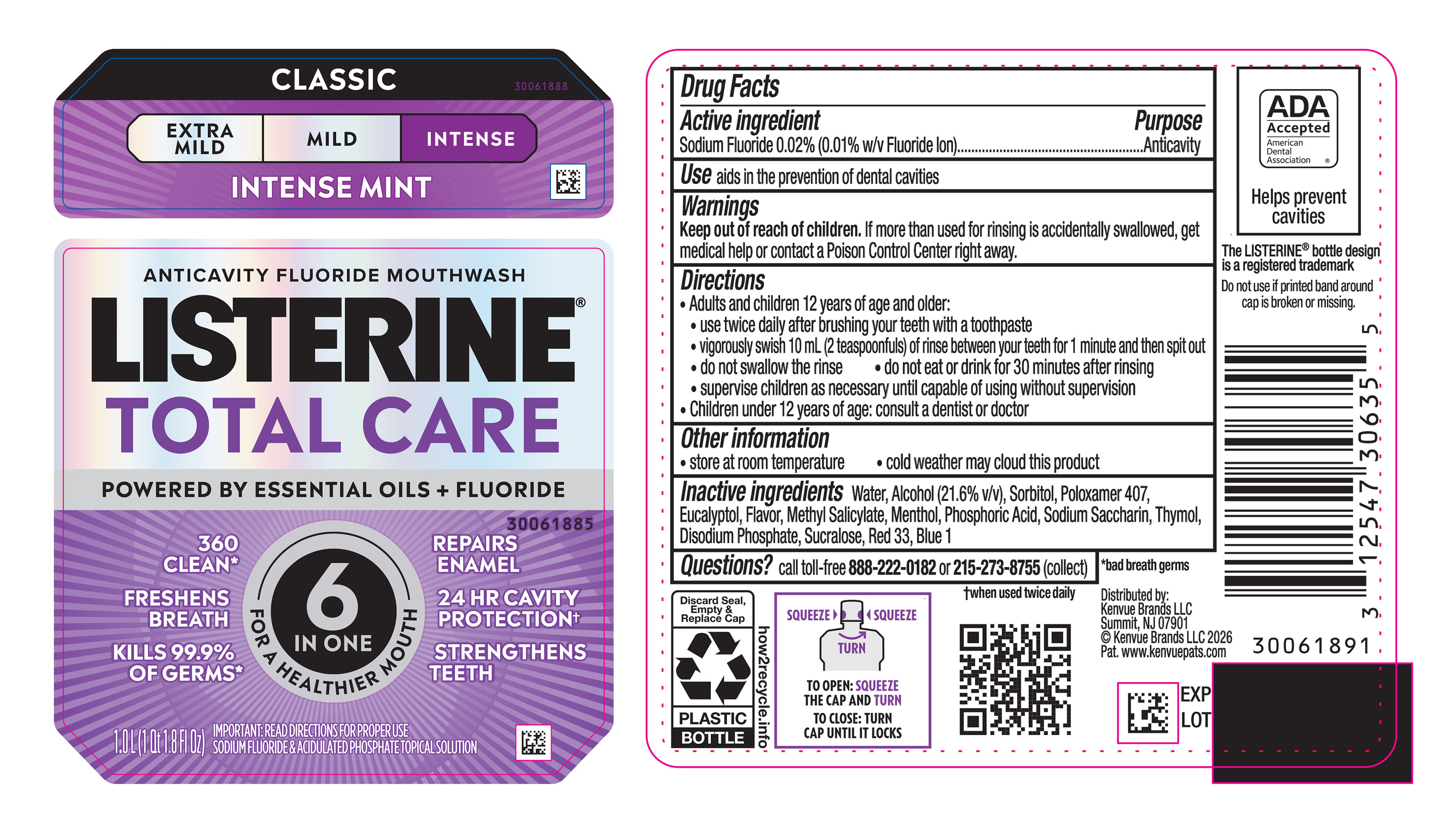 DRUG LABEL: Listerine Total Care Intense Anticavity Fluoride Mouthwash
NDC: 69968-0952 | Form: MOUTHWASH
Manufacturer: Kenvue Brands LLC
Category: otc | Type: HUMAN OTC DRUG LABEL
Date: 20260218

ACTIVE INGREDIENTS: SODIUM FLUORIDE 0.1 mg/1 mL
INACTIVE INGREDIENTS: ALCOHOL; WATER; PHOSPHORIC ACID; POLOXAMER 407; EUCALYPTOL; METHYL SALICYLATE; SORBITOL; RED 33; MENTHOL; DISODIUM PHOSPHATE; BLUE 1; THYMOL; SUCRALOSE; SODIUM SACCHARIN

Listerine Total Care Intense Anticavity Fluoride Mouthwash

Drug Facts

Active ingredient

Sodium Fluoride 0.02% (0.01% w/v Fluoride ion)

Purpose

Anticavity

Use

aids in the prevention of dental cavities

Warnings

Keep out of reach of children . If more than used for rinsing is accidentally swallowed, get medical help or contact a Poison Control Center right away.

Directions

• Adults and children 12 years of age and older:

• Use twice daily after brushing your teeth with a toothpaste

• vigorously swish 10 mL (2 teaspoonfuls) of rinse between your teeth for 1 minute and then spit out

• do not swallow the rinse

• do not eat or drink for 30 minutes after rinsing

• supervise children as necessary until capable of using without supervision

• Children under 12 years of age: consult a dentist or doctor

Other information

• store at room temperature

• cold weather may cloud this product

Inactive ingredients

Water, Alcohol (21.6% v/v), Sorbitol, Poloxamer 407, Eucalyptol, Flavor, Methyl Salicylate, Menthol, Phosphoric Acid, Sodium Saccharin, Thymol, Disodium Phosphate, Sucralose, Red 33, Blue 1

Questions?

call toll-free 888-222-0182; or 215-273-8755 (collect)

Distributed by:
Kenvue Brands LLC
Summit, NJ 07901

PRINCIPAL DISPLAY PANEL - 1 L Bottle Label

ANTICAVITY FLUORIDE MOUTHWASH

LISTERINE®

TOTAL CARE

POWERED BY ESSENTIAL OILS + FLUORIDE

6

IN ONE

FOR A HEALTHIER MOUTH

360

CLEAN*

FRESHENS

BREATH

KILLS 99.9%

OF GERMS*

REPAIRS

ENAMEL

24 HR CAVITY

PROTECTION†

STRENGTHENS

TEETH

IMPORTANT: READ DIRECTIONS FOR PROPER USE

SODIUM FLUORIDE & ACIDULATED PHOSPHATE TOPICAL SOLUTION

1.0 L (1 Qt 1.8 FL Oz)